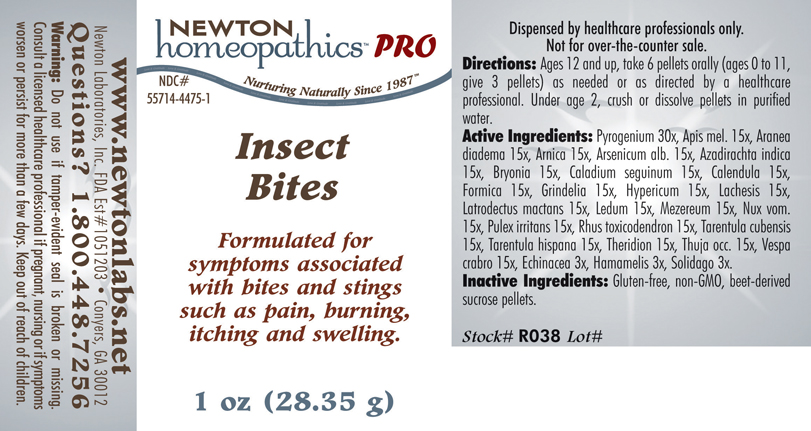 DRUG LABEL: Insect Bites 
NDC: 55714-4475 | Form: PELLET
Manufacturer: Newton Laboratories, Inc.
Category: homeopathic | Type: HUMAN PRESCRIPTION DRUG LABEL
Date: 20110601

ACTIVE INGREDIENTS: Rancid Beef 30 [hp_X]/1 g; Apis Mellifera 15 [hp_X]/1 g; Araneus Diadematus 15 [hp_X]/1 g; Arnica Montana 15 [hp_X]/1 g; Arsenic Trioxide 15 [hp_X]/1 g; Azadirachta Indica Bark 15 [hp_X]/1 g; Bryonia Alba Root 15 [hp_X]/1 g; Dieffenbachia Seguine 15 [hp_X]/1 g; Calendula Officinalis Flowering Top 15 [hp_X]/1 g; Formica Rufa 15 [hp_X]/1 g; Grindelia Hirsutula Flowering Top 15 [hp_X]/1 g; Hypericum Perforatum 15 [hp_X]/1 g; Lachesis Muta Venom 15 [hp_X]/1 g; Latrodectus Mactans 15 [hp_X]/1 g; Ledum Palustre Twig 15 [hp_X]/1 g; Daphne Mezereum Bark 15 [hp_X]/1 g; Strychnos Nux-vomica Seed 15 [hp_X]/1 g; Pulex Irritans 15 [hp_X]/1 g; Toxicodendron Pubescens Leaf 15 [hp_X]/1 g; Citharacanthus Spinicrus 15 [hp_X]/1 g; Lycosa Tarantula 15 [hp_X]/1 g; Theridion Curassavicum 15 [hp_X]/1 g; Thuja Occidentalis Leafy Twig 15 [hp_X]/1 g; Vespa Crabro 15 [hp_X]/1 g; Echinacea, Unspecified 3 [hp_X]/1 g; Hamamelis Virginiana Root Bark/stem Bark 3 [hp_X]/1 g; Solidago Virgaurea Flowering Top 3 [hp_X]/1 g
INACTIVE INGREDIENTS: Sucrose

Insect Bites

INDICATIONS & USAGE SECTION

Insect Bites Formulated for symptoms associated with bites and stings such as pain, burning, itching and swelling.

DOSAGE & ADMINISTRATION SECTION

Directions: Ages 12 and up, take 6 pellets orally (ages 0 to 11, give 3 pellets) as needed or as directed by a healthcare professional. Under age 2, crush of dissolve pellets in purified water.

ACTIVE INGREDIENT SECTION

Pyrogenium 30x, Apis mel. 15x, Aranea diadema 15x, Arnica 15x, Arsenicum alb 15x, Azadirachta indica 15x, Bryonia 15x, Caladium seguinum 15x, Calendula 15x, Formica 15x, Grindelia 15x, Hypericum 15x, Lachesis 15x, Latrodectus mactans 15x, Ledum 15x, Mezereum 15x, Nux vom. 15x, Pulex irritans 15x, Rhus toxicodendron 15x, Tarentula cubensis 15x, Tarentula hispana 15x, Theridion 15x, Thuja occ. 15x, Vespa crabro 15x, Echinacea 3x, Hamamelis 3x, Solidago 3x.

PURPOSE SECTION

Formulated for symptoms associated with bites and stings such as pain, burning, itching and swelling.

INACTIVE INGREDIENT SECTION

Gluten-free, non-GMO, beet-derived sucrose pellets.

QUESTIONS? SECTION

www.newtonlabs.net Newton Laboratories, Inc. FDA Est # 1051203 - Conyers, GA 30012
Questions? 1.800.448.7256

WARNINGS SECTION

Warning: Do not use if tamper - evident seal is broken or missing. Consult a licensed healthcare professional if pregnant, nursing or if symptoms worsen or persist for more than a few days. Keep out of reach of children.

PREGNANCY OR BREAST FEEDING SECTION

Consult a licensed healthcare professional if pregnant or nursing or if symptoms worsen or persist for more than a few days.

KEEP OUT OF REACH OF CHILDREN SECTION

Keep out of reach of children.